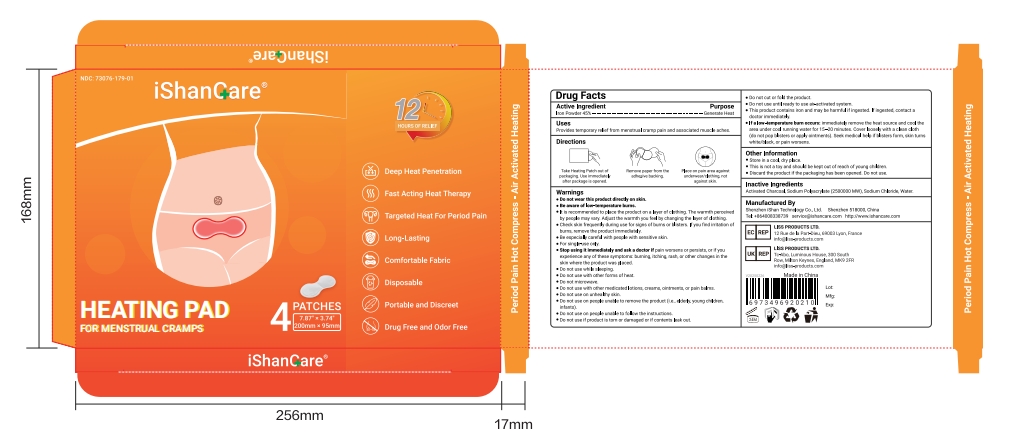 DRUG LABEL: iShanCare Heating Pad
NDC: 73076-179 | Form: PATCH
Manufacturer: Shenzhen Ishan Technology Co., Ltd
Category: homeopathic | Type: HUMAN OTC DRUG LABEL
Date: 20260212

ACTIVE INGREDIENTS: IRON POWDER 45 g/100 g
INACTIVE INGREDIENTS: ACTIVATED CHARCOAL; SODIUM POLYACRYLATE (2500000 MW); SODIUM CHLORIDE; WATER

Active ingredient

Iron Powder 45%

Inactive ingredient

Activated Charcoal, Sodium Polyacrylate (2500000 MW), Sodium Chloride, Water.

Keep out of reach of children.

if swallowed, call poison control or seek medical help.

Stop use and ask a doctor if

pain worsens or persists, or if youexperience any of these symptoms: burning, itching, rash, or other changes in theskin where the product was placed.

USES

Provides temporary relief from menstrual cramp pain and associated muscle aches.

Other information

Store in a cool, dry place.
This is not a toy and should be kept out of reach of young children.

Discard the product if the packaging has been opened. Do not use.

Directions

Take Heating Patch out ofpackaging.Use immediatelyafter package is opened.

Remove paper from theadhesive backing.

Place on pain area againsunderwear/clothing, not against skin.

Dosage & administration

Apply as needed

When using this product

Do not wear this product directly on skin.

Be aware of low-temperature burns.

Warning

For external use only. Do not wear this product directly on skin.

RECENT MAJOR CHANGES

no